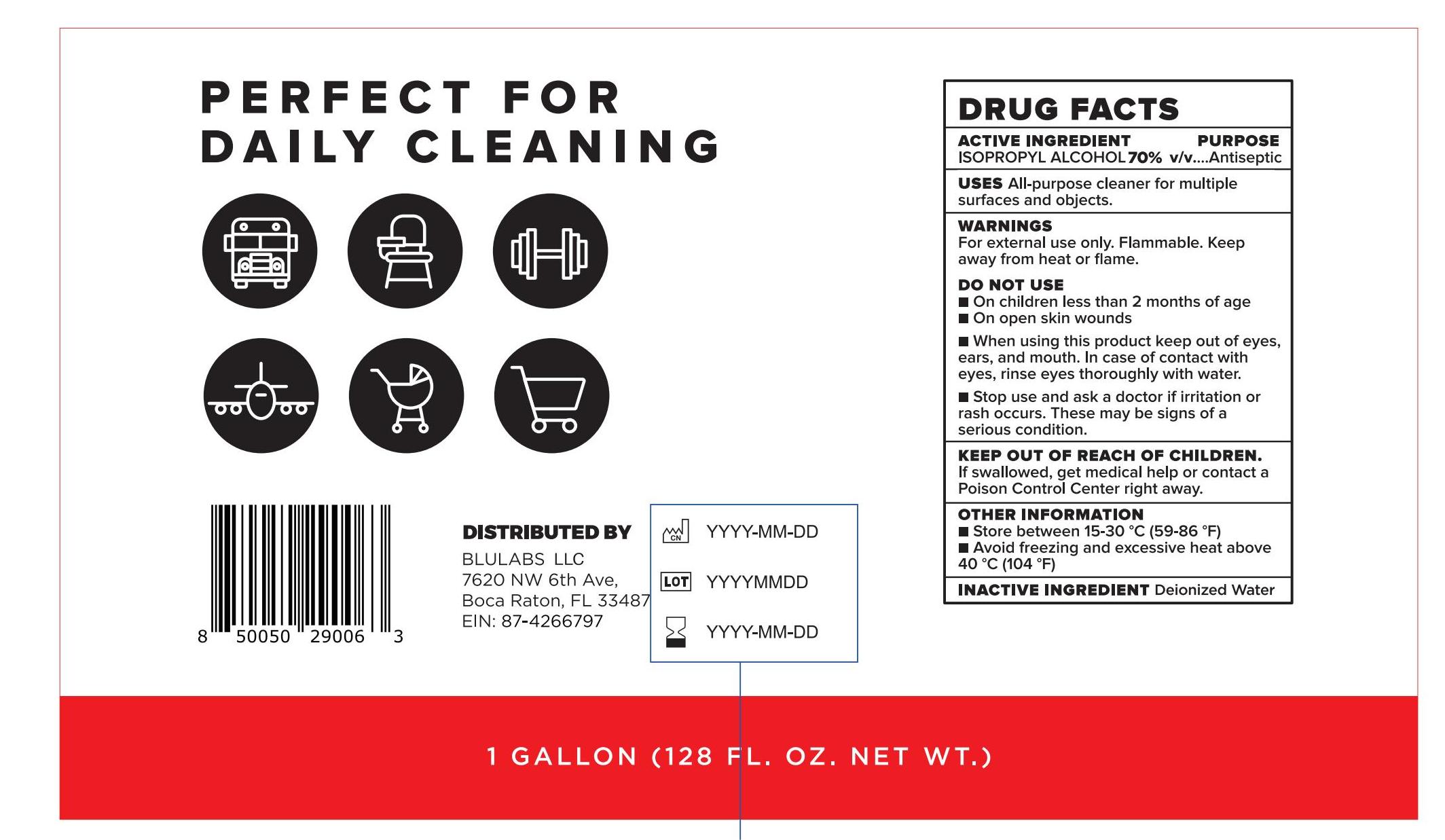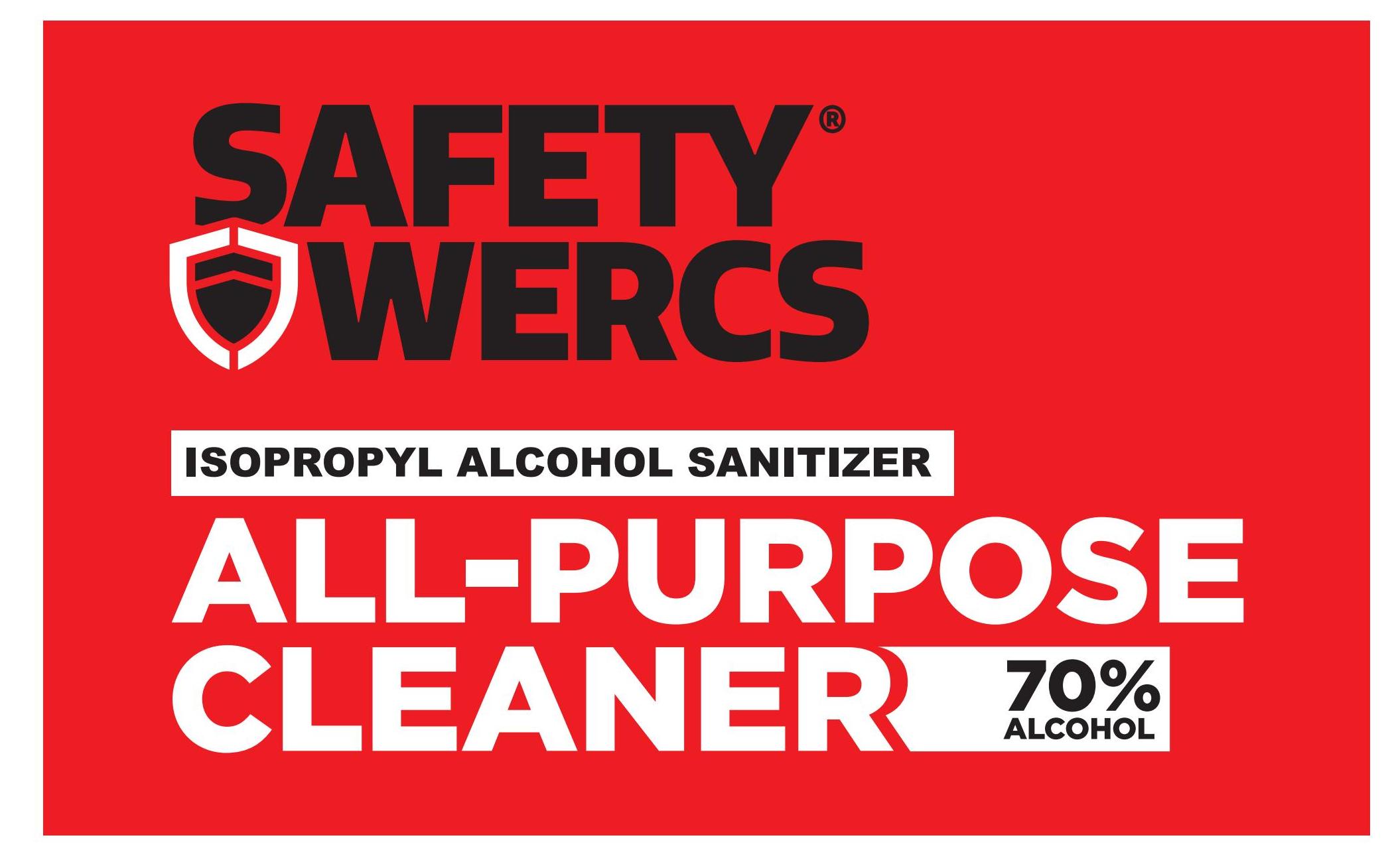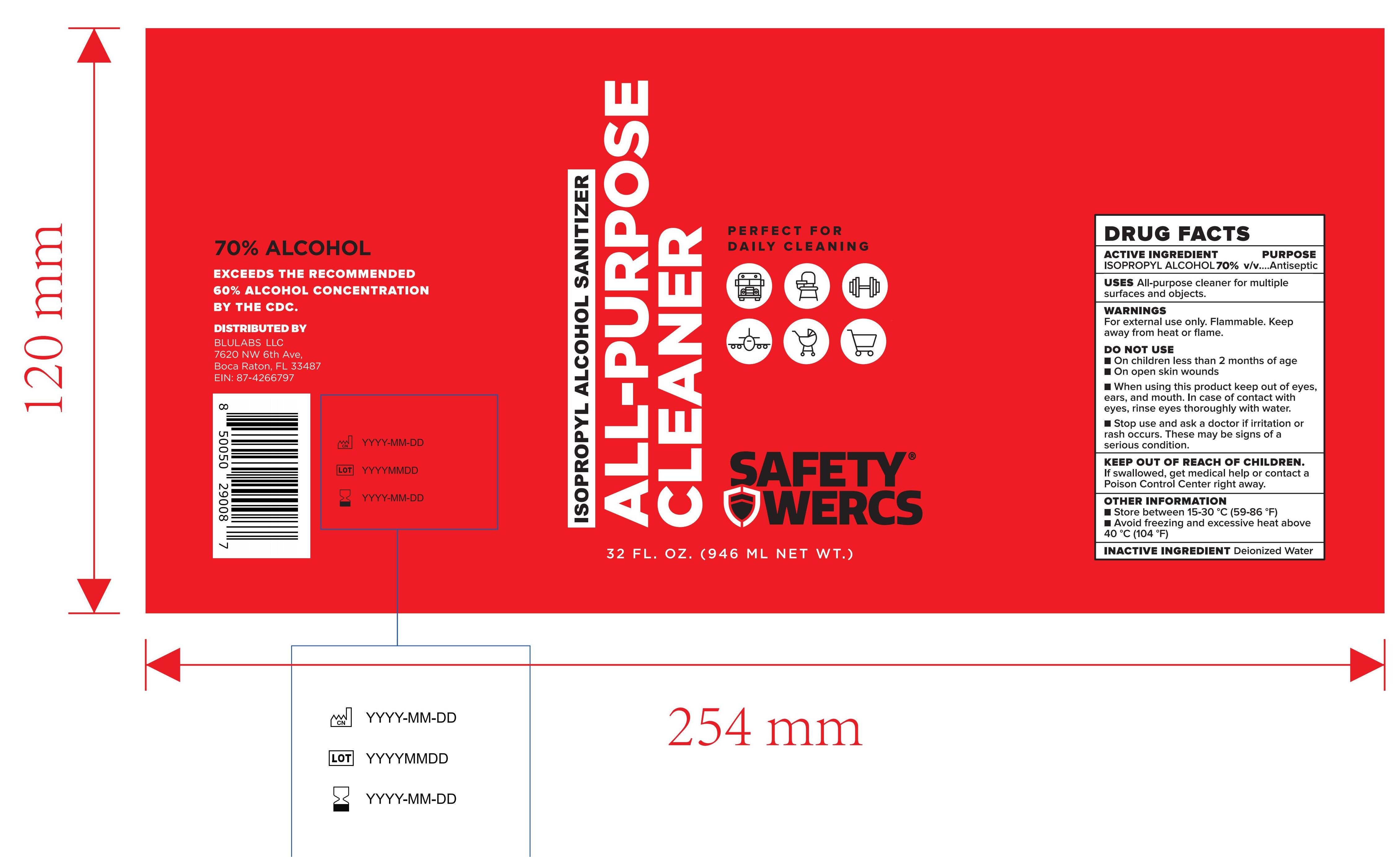 DRUG LABEL: Isopropyl Alcohol Sanitizer
NDC: 84354-103 | Form: SOLUTION
Manufacturer: safety wercs
Category: otc | Type: HUMAN OTC DRUG LABEL
Date: 20240626

ACTIVE INGREDIENTS: ISOPROPYL ALCOHOL 70 mL/100 mL
INACTIVE INGREDIENTS: WATER 30 mL/100 mL

Isopropyl Alcohol Sanitizer

Active Ingredient

Isopropyl Alcohol:70%(v/v)

Purpose

Antiseptic

Uses

All-purpose cleaner for multiple surfaces and objects.

WARNINGS

For external use only.

Flammable.

Keep away from heat or flame.

Do not use

On children less than 2 months of age

On open skin wounds

When using this product keep out of eyes,ears, and mouth. In case of contact with eyes, rinse eyes thoroughly with water.

Stop use and ask a doctor if irritation or rash occurs. These may be signs of a serious condition.

Keep out of reach of children

If swallowed, get medical help or contact a Poison Control Center right away.

Other Information

Store between 15-30°C (59-86°F)

Avoid freezing and excessive heat above 40°C(104°F)

Inactive Ingredient

Deionized Water

Uses

All-purpose cleaner for multiple surfaces and objects